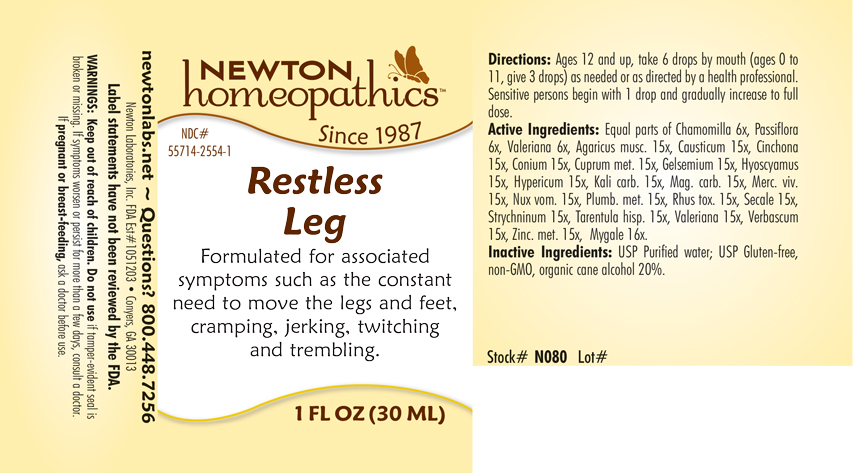 DRUG LABEL: Restless Leg
NDC: 55714-2554 | Form: LIQUID
Manufacturer: Newton Laboratories, Inc.
Category: homeopathic | Type: HUMAN OTC DRUG LABEL
Date: 20250210

ACTIVE INGREDIENTS: AMANITA MUSCARIA FRUITING BODY 15 [hp_X]/1 mL; AVICULARIA AVICULARIA 16 [hp_X]/1 mL; CAUSTICUM 15 [hp_X]/1 mL; CINCHONA OFFICINALIS BARK 15 [hp_X]/1 mL; CONIUM MACULATUM FLOWERING TOP 15 [hp_X]/1 mL; COPPER 15 [hp_X]/1 mL; GELSEMIUM SEMPERVIRENS ROOT 15 [hp_X]/1 mL; HYOSCYAMUS NIGER 15 [hp_X]/1 mL; HYPERICUM PERFORATUM 15 [hp_X]/1 mL; POTASSIUM CARBONATE 15 [hp_X]/1 mL; MAGNESIUM CARBONATE 15 [hp_X]/1 mL; MERCURY 15 [hp_X]/1 mL; STRYCHNOS NUX-VOMICA SEED 15 [hp_X]/1 mL; LEAD 15 [hp_X]/1 mL; TOXICODENDRON PUBESCENS LEAF 15 [hp_X]/1 mL; CLAVICEPS PURPUREA SCLEROTIUM 15 [hp_X]/1 mL; STRYCHNINE 15 [hp_X]/1 mL; LYCOSA TARANTULA 15 [hp_X]/1 mL; VALERIAN 15 [hp_X]/1 mL; VERBASCUM THAPSUS 15 [hp_X]/1 mL; ZINC 15 [hp_X]/1 mL; MATRICARIA CHAMOMILLA 6 [hp_X]/1 mL; PASSIFLORA INCARNATA FLOWERING TOP 6 [hp_X]/1 mL
INACTIVE INGREDIENTS: ALCOHOL; WATER

Restless 2554L

INDICATIONS & USAGE SECTION

Formulated for associated symptoms such as the constant need to move the legs and feet, cramping, jerking, twitching and trembling.

DOSAGE & ADMINISTRATION SECTION

Directions: Ages 12 and up, take 6 drops by mouth (ages 0 to 11, give 3 drops) as needed or as directed by a health professional. Sensitive persons being with 1 drop and gradually increase to full dose.

OTC - ACTIVE INGREDIENT SECTION

Equal parts of Chamomilla 6x, Passiflora incarnata 6x, Valeriana officinalis 6x, Agaricus muscarius 15x, Causticum 15x, Cinchona officinalis 15x, Conium maculatum 15x, Cuprum metallicum 15x, Gelsemium sempervirens 15x, Hyoscyamus niger 15x, Hypericum perforatum 15x, Kali carbonicum 15x, Magnesia carbonica 15x, Mercurius vivus 15x, Nux vomica 15x, Plumbum metallicum 15x, Rhus toxicodendron 15x, Secale cornutum 15x, Strychninum 15x, Tarentula hispana 15x, Valeriana officinalis 15x, Verbascum thapsus 15x, Zincum metallicum 15x, Mygale 16x.

OTC - PURPOSE SECTION

Formulated for associated symptoms such as the constant need to move the legs and feet, cramping, jerking, twitching and trembling.

INACTIVE INGREDIENT SECTION

Inactive Ingredients: USP Purified Water; USP Gluten-free, non-GMO, organic cane alcohol 20%.

QUESTIONS SECTION

newtonlabs.net – Questions? 800.448.7256

Newton Laboratories, Inc. FDA Est # 1051203 - Conyers, GA 30013

WARNINGS SECTION

WARNINGS: Keep out of reach of children. Do not use if tamper-evident seal is broken or missing. If symptoms worsen or persist for more than a few days, consult a doctor. If pregnant or breast-feeding, ask a doctor before use.

OTC - PREGNANCY OR BREAST FEEDING SECTION

If pregnant or breast-feeding, ask a doctor before use.

OTC - KEEP OUT OF REACH OF CHILDREN SECTION

Keep out of reach of children